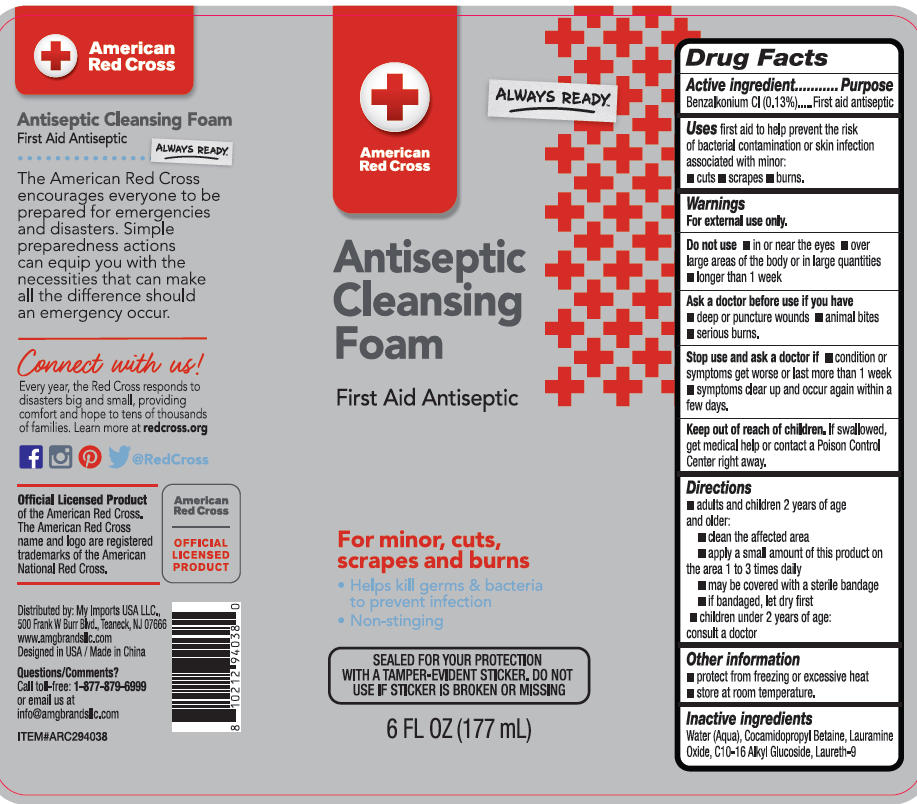 DRUG LABEL: AMERICAN RED CROSS ANTISEPTIC CLEANSING FOAM
NDC: 75742-082 | Form: LIQUID
Manufacturer: Zhejiang Guoyao Jingyue Aerosol Co., Ltd.
Category: otc | Type: HUMAN OTC DRUG LABEL
Date: 20260210

ACTIVE INGREDIENTS: BENZALKONIUM CHLORIDE 0.13 g/100 mL
INACTIVE INGREDIENTS: LAURAMINE OXIDE; POLIDOCANOL; WATER; COCAMIDOPROPYL BETAINE; .BETA.-D-GLUCOPYRANOSE

AMERICAN RED CROSS ANTISEPTIC CLEANSING FOAM

Active ingredient

Benzalkonium Cl 0.13% v/v

Purpose

First aid antiseptic

Uses

first aid to help prevent the risk of bacterial contamination or skin infection associated with minor:cuts, scrapes, burns

Warning

For external use only

Do not use

- in or near the eyes
- over large areas of the body or in large quantities
- longer than 1 week

Ask a doctor before use if you have

- deep or puncture wounds
- animal bites
- serious burns

Keep out of reach of children

If swallowed, get medical help or contact a Poison Control Center right away.

Directions

- adults and children 2 years of age and older:
- clean the affected area
- apply a small amount of this product on the area 1 to 3 times daily
- may be covered with a sterile bandage
- if bandaged, let dry first
- children under 2 years of age: consult a doctor

Other Information

- protect from freezing or excessive heat
- store at room temperature.

Inactive ingredients

Water(Auqa)

COCAMIDOPROPYL BETAINE

LAURAMINE OXIDE

C10-16 ALKYL GLUCOSIDE

LAURETH-9